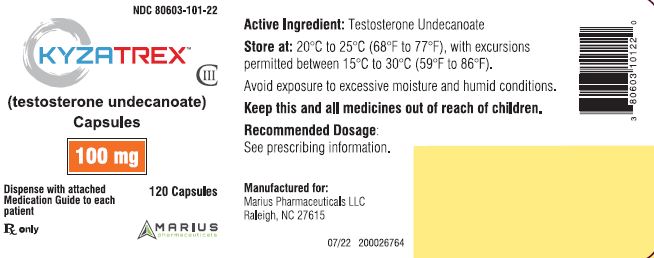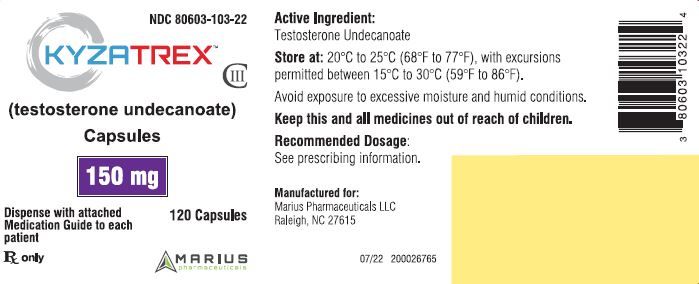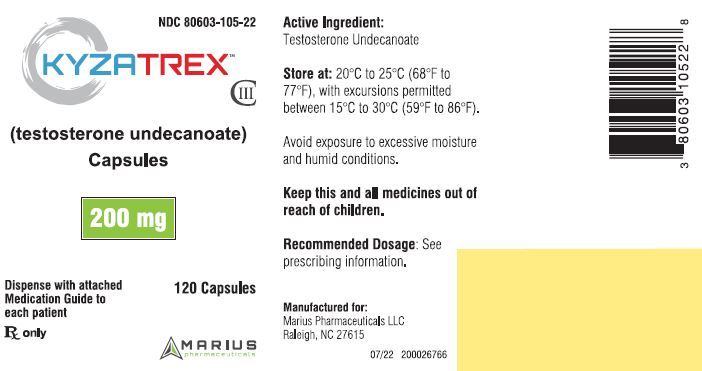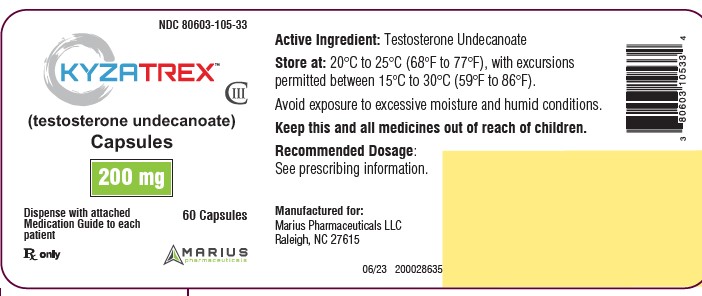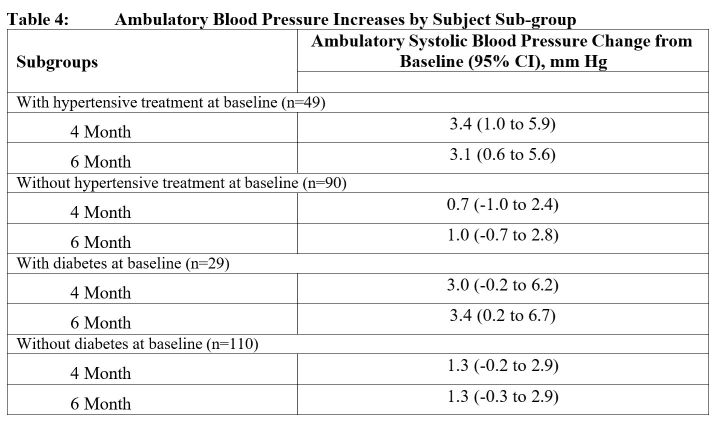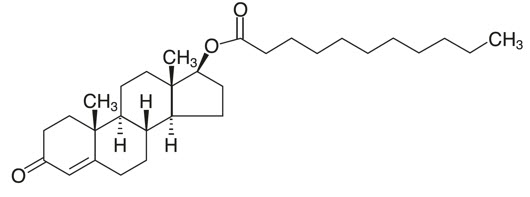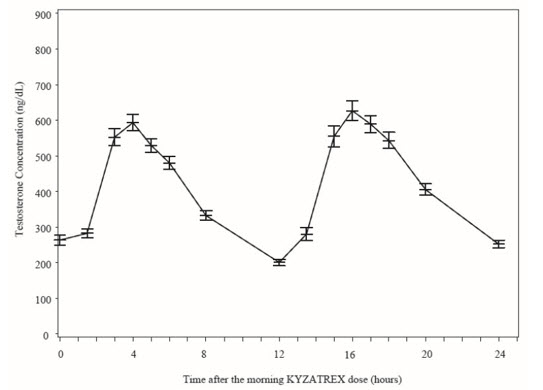 DRUG LABEL: Kyzatrex
NDC: 80603-101 | Form: CAPSULE, LIQUID FILLED
Manufacturer: Marius Pharmaceuticals
Category: prescription | Type: HUMAN PRESCRIPTION DRUG LABEL
Date: 20251015
DEA Schedule: CIII

ACTIVE INGREDIENTS: TESTOSTERONE UNDECANOATE 100 mg/1 1
INACTIVE INGREDIENTS: PROPYLENE GLYCOL MONOLAURATE; POLYOXYL 40 HYDROGENATED CASTOR OIL; .ALPHA.-TOCOPHEROL; GELATIN, UNSPECIFIED; SORBITOL; GLYCERIN; WATER; TITANIUM DIOXIDE

HIGHLIGHTS OF PRESCRIBING INFORMATION

These highlights do not include all the information needed to use KYZATREX® safely and effectively. See full prescribing information for KYZATREX®.
KYZATREX® (testosterone undecanoate) capsules, for oral use, CIII Initial U.S. approval: 1953

1 INDICATIONS AND USAGE

KYZATREX® is an androgen indicated for testosterone replacement therapy in adult males for conditions associated with a deficiency or absence of endogenous testosterone (1).

Limitations of Use:

- Safety and efficacy of KYZATREX® in males less than 18 years old have not been established (1, 8.4).
- Safety and efficacy of KYZATREX® in men with “age-related hypogonadism” have not been established (1).

2 DOSAGE AND ADMINISTRATION

- KYZATREX® is not substitutable with other oral testosterone undecanoate products (2.1).
- Prior to initiating KYZATREX®, confirm the diagnosis of hypogonadism by ensuring that serum testosterone concentrations have been measured in the morning on at least two separate days and that these concentrations are below the normal range (2.2).
- Take KYZATREX® with food (2.3).
- Starting dosage: 200 mg orally once in the morning and once in the evening (2.3).
- Adjust the dosage to a minimum of 100 mg once in the morning and a maximum of 400 mg twice daily based on serum testosterone drawn 3 to 5 hours after the morning dose at least 7 days after starting treatment or following dose adjustment and periodically thereafter (2.3).

3 DOSAGE FORMS AND STRENGTHS

Capsules: 100 mg, 150 mg, 200 mg (3).

4 CONTRAINDICATIONS

- Carcinoma of the breast or known or suspected carcinoma of the prostate (5.4)
- Women who are pregnant. Testosterone may cause fetal harm (4, 5.7, 8.1)
- Hypersensitivity to KYZATREX® or any of its ingredients (4)

5 WARNINGS AND PRECAUTIONS

- Polycythemia: Monitor hemoglobin or hematocrit approximately every 3 months to detect increased red blood cell mass and polycythemia. Discontinue KYZATREX® if necessary (5.1).
- Venous thromboembolism (VTE): VTE, including deep vein thrombosis (DVT) and pulmonary embolism (PE) have been reported in patients using testosterone. Discontinue KYZATREX® if VTE is suspected and initiate appropriate workup and management (5.2)
- Worsening of Benign Prostatic Hyperplasia (BPH) and Potential Risk of Prostate Cancer: Monitor patients for worsening of signs and symptoms of BPH. Evaluate patients for prostate cancer, including monitoring prostate specific antigen (PSA) prior to initiating and during treatment with androgens (5.3).
- Blood Pressure Increases: KYZATREX® can increase blood pressure, which can increase cardiovascular risk over time. Measure blood pressure periodically. Not recommended for use in men with uncontrolled hypertension (5.4)
- Abuse of Testosterone and Monitoring of Serum Testosterone: If testosterone use at doses higher than recommended for the approved indication and in combination with other anabolic androgenic steroids is suspected, check serum testosterone concentration (5.5).
- Potential for Adverse Effects on Spermatogenesis: KYZATREX® may cause azoospermia (5.7).
- Edema: Edema, with or without congestive heart failure (CHF), may occur in patients with pre-existing cardiac, renal, or hepatic disease. Discontinue KYZATREX® and initiate appropriate workup (5.9).
- Sleep Apnea: KYZATREX® may potentiate sleep apnea in those with risk factors (5.10)
- Lipid Changes: KYZATREX® may affect serum lipid profile. Monitor patient lipid concentrations periodically; if necessary, adjust dosage of lipid lowering drug(s) or discontinue KYZATREX® (5.12).

6 ADVERSE REACTIONS

Most common adverse reactions (incidence ≥ 2%): hypertension (6.1).

To report SUSPECTED ADVERSE REACTIONS, contact Marius Pharmaceuticals at 1-833-949-5040 or FDA at 1-800-FDA-1088 or www.fda.gov/medwatch.

7 DRUG INTERACTIONS

- Insulin: In patients with diabetes, concomitant use with KYZATREX® may decrease blood glucose and insulin requirements (7.1).
- Oral Anticoagulants: Concomitant use with KYZATREX® may cause changes in anticoagulant activity. Monitor International Normalized Ratio (INR) and prothrombin time (PT) frequently (7.2).
- Corticosteroids: Concomitant use with KYZATREX® may result in increased fluid retention. Use with caution, particularly in patients with cardiac, renal, or hepatic disease (7.3).
- Drugs that May Also Increase Blood Pressure: Concomitant use with KYZATREX® may lead to additional increases in blood pressure (7.4).

8 USE IN SPECIFIC POPULATIONS

Geriatric Patients: Geriatric patients treated with androgens may also be at risk for worsening of signs and symptoms of BPH and hypertension (8.5).

Recent Major Changes

Boxed Warnings, Blood Pressure Increases Removed 07/2025

Contraindications, Hypogonadal conditions not

associated with structural or genetic etiologies (4), Removed 07/2025

Warnings and Precautions, Venous Thromboembolism (5.2) 07/2025

Warnings and Precautions, Blood Pressure Increases (5.4) 07/2025

Warnings and Precautions, Cardiovascular Risk (5.4) Removed 07/2025

FULL PRESCRIBING INFORMATION

1 INDICATIONS AND USAGE

KYZATREX® is indicated for testosterone replacement therapy in adult males for conditions associated with a deficiency or absence of endogenous testosterone:

- Primary hypogonadism (congenital or acquired): testicular failure due to conditions such as cryptorchidism, bilateral torsion, orchitis, vanishing testis syndrome, orchiectomy, Klinefelter syndrome, chemotherapy, or toxic damage from alcohol or heavy metals. These men usually have low serum testosterone concentrations and gonadotropins (folliclestimulating hormone (FSH), luteinizing hormone (LH)) above the normal range.
- Hypogonadotropic hypogonadism (congenital or acquired): gonadotropin or luteinizing hormone-releasing hormone (LHRH) deficiency, pituitary-hypothalamic injury from tumors, trauma, or radiation. These men have low serum testosterone concentrations but have gonadotropins in the normal or low range.

Limitations of Use

Safety and efficacy of KYZATREX® in males less than 18 years old have not been established [see Use in Specific Populations (8.4)] .

Safety and efficacy of KYZATREX® in men with “age-related hypogonadism” (also referred to as “late-onset hypogonadism”) have not been established.

2 DOSAGE AND ADMINISTRATION

-

2.1 Important Dosage Information

KYZATREX® is not substitutable with other oral testosterone undecanoate products.

2.2 Confirmation of Hypogonadism Before Initiation of KYZATREX®

Prior to initiating KYZATRE®, confirm the diagnosis of hypogonadism by ensuring that serum testosterone concentrations have been measured in the morning on at least two separate days and that these testosterone concentrations are below the normal range.

2.3 Recommended Dosage and Administration

Individualize the dosage of KYZATREX® based on the patient's serum testosterone concentration response to the drug.

The recommended starting dose is 200 mg orally twice daily, once in the morning and once in the evening. Take KYZATREX® with food.

Dosage Adjustment

Check serum testosterone concentrations 7 days after starting treatment or after dosage adjustment, 3 to 5 hours after the morning dose. Adjust the KYZATREX® dose as necessary as shown in Table 1. Thereafter, periodically monitor serum testosterone concentrations.

The minimum recommended dose is 100 mg once daily in the morning. The maximum recommended dose is 400 mg twice daily. For total daily doses greater than 100 mg, administer the same dose in the morning and evening.

Table 1: KYZATREX® Dosage Adjustment Scheme
Serum Testosterone Concentration | Current KYZATREX® Dosage | New KYZATREX® Dosage
Less than 460 ng/dL | 100 mg with breakfast only | 100 mg twice daily with meals
Less than 460 ng/dL | 100 mg twice daily with meals | 200 mg twice daily with meals
Less than 460 ng/dL | 200 mg twice daily with meals | 300 mg twice daily with meals
Less than 460 ng/dL | 300 mg twice daily with meals | 400 mg twice daily with meals
460 to 971 ng/dL | No Dosage Change
More than 971 ng/dL | 400 mg twice daily with meals | 300 mg twice daily with meals
More than 971 ng/dL | 300 mg twice daily with meals | 200 mg twice daily with meals
More than 971 ng/dL | 200 mg twice daily with meals | 100 mg twice daily with meals
More than 971 ng/dL | 100 mg twice daily with meals | 100 mg with breakfast only
More than 971 ng/dL | 100 mg with breakfast only | Discontinue treatment

3 DOSAGE FORMS AND STRENGTHS

Capsules:

- 100 mg, oval, opaque, white, imprinted with "MP100" in red ink
- 150 mg, oblong, opaque, white, imprinted with "MP150" in red ink
- 200 mg, oblong, opaque, white, imprinted with "MP200" in red ink

4 CONTRAINDICATIONS

KYZATREX® is contraindicated in:

- Patients with carcinoma of the breast or known or suspected carcinoma of the prostate [see Warnings and Precautions (5.34)] .
- Women who are pregnant. Testosterone can cause virilization of the female fetus when administered to a pregnant woman [ see Use in Specific Populations (8.1)].
- Patients with known hypersensitivity to KYZATREX® or any of its ingredients [see Description (11)] .

5 WARNINGS AND PRECAUTIONS

-

5.1 Polycythemia

Androgens, including KYZATREX®, can cause increase in hemoglobin or hematocrit, reflective of increase in red blood cell mass. Check hematocrit prior to initiating KYZATREX®. An increase in red blood cell mass may increase the risk of thromboembolic events [see Warnings and Precautions (5.2)]. Evaluate hematocrit approximately every 3 months while the patient is on KYZATREX®. If hematocrit becomes elevated, stop KYZATREX® until the hematocrit decreases to an acceptable concentration. If KYZATREX® is restarted and again causes hematocrit to become elevated, permanently discontinue KYZATREX®.

5.2 Venous Thromboembolism

There have been post-marketing reports of venous thromboembolic events, including deep vein thrombosis (DVT) and pulmonary embolism (PE), in patients using testosterone replacement products such as KYZATREX®.

In the Testosterone Replacement therapy for Assessment of long-term Vascular Events and efficacy Response in hypogonadal men (TRAVERSE) Study, a randomized, double-blind, placebo-controlled, cardiovascular (CV) outcomes study, compared to placebo, topical testosterone gel was associated with a numerically higher incidence of VTE (1.7% vs 1.2%) which included DVT (0.6% vs 0.5%) and PE events (0.9% vs 0.5%) [see Adverse Reactions 6.1)].

Evaluate patients who report symptoms of pain, edema, warmth, and erythema in the lower extremity for DVT and those who present with acute shortness of breath for PE. If a venous thromboembolic event is suspected, discontinue KYZATREX® and initiate appropriate workup and management [see Adverse Reactions (6.2)].

5.3 Worsening of Benign Prostatic Hyperplasia (BPH) and Potential Risk of Prostate Cancer

- Patients with BPH who are treated with androgens are at an increased risk for worsening of signs and symptoms of BPH. Monitor patients with BPH for worsening signs and symptoms.
- Patients treated with androgens may be at increased risk for prostate cancer. Evaluate patients for prostate cancer prior to initiating and during treatment with androgens [see Contraindications (4)].

5.4 Blood Pressure Increases

KYZATREX® can increase blood pressure. Based on ambulatory blood monitoring in Study MRS-TU-2019EXT, KYZATREX® increased mean systolic/diastolic blood pressure by 1.7/0.6 mm Hg from baseline after 4 months of treatment and 1.8/0.6 mm Hg from baseline after 6 months of treatment [see Adverse Reactions (6.1)]. In patients with hypertension on antihypertensive therapy, KYZATREX® increased the mean systolic/diastolic BP by 3.4/0.7 mm Hg from baseline after 4 months of treatment and 3.1/1.0 mm Hg from baseline after 6 months of treatment. [see Adverse Reactions (6.1)]. Blood pressure increases can increase cardiovascular (CV) risk over time.

The CV risk associated with topical testosterone gel was evaluated in TRAVERSE, a randomized, double-blind, placebo controlled, CV outcomes study in men with a history of CV disease or multiple CV risk factors. In TRAVERSE, topical testosterone gel increased mean systolic blood pressure by 1.0 mm Hg from baseline to 36 months, whereas a mean decrease from baseline of 0.5 mm Hg. However, the incidences of major adverse cardiovascular events (MACE), including cardiovascular death, non-fatal myocardial infarction [MI] and non-fatal stroke, were similar between treatment groups (7% for topical testosterone gel vs 7.3% for placebo) [See Adverse Reactions (6.1)]

Monitor BP periodically in men using KYZATREX®, especially men with hypertension. KYZATREX® is not recommended for use in patients with uncontrolled hypertension.

5.5 Abuse of Testosterone and Monitoring of Testosterone Centrations.

Testosterone has been subject to abuse, typically at doses higher than recommended for the approved indication and in combination with other anabolic androgenic steroids. Anabolic androgenic steroid abuse can lead to serious cardiovascular and psychiatric adverse reactions [see Drug Abuse and Dependence (9)].

If testosterone abuse is suspected, check testosterone concentrations to ensure they are within therapeutic range [see Dosage and Administration (2.2)]. Testosterone levels may remain in the normal or subnormal range in men abusing synthetic testosterone derivatives. Counsel patients concerning the serious adverse reactions associated with abuse of testosterone and anabolic androgenic steroids. Also consider the possibility of testosterone and anabolic androgenic steroid abuse in suspected patients who present with serious cardiovascular or psychiatric adverse events.

5.6 Not for Use In Women

Due to lack of controlled studies in women and potential virilizing effects, KYZATREX® is not indicated for use in women [see Contraindications (4) and Use in Specific Populations (8.1, 8.2)].

5.7 Potential for Adverse Effects on Spermatogenesis

With large doses of exogenous androgens, including KYZATREX®, spermatogenesis may be suppressed through feedback inhibition of pituitary FSH, possibly leading to adverse effects on semen parameters including sperm count [see Use in Specific Populations (8.3)]. Inform patients of this possible risk when deciding whether to use or to continue to use KYZATREX®.

5.8 Hepatic Adverse Effects

KYZATREX® is not a 17-alpha-alkyl androgen and is not known to cause hepatic adverse effects. However, prolonged use of high doses of orally active 17-alpha-alkyl androgens (e.g., methyltestosterone) has been associated with serious hepatic adverse effects (peliosis hepatis, hepatic neoplasms, cholestatic hepatitis, and jaundice). Peliosis hepatis can be a life-threatening or fatal complication. Long-term therapy with intramuscular testosterone enanthate has produced multiple hepatic adenomas. Patients should be instructed to report any signs or symptoms of hepatic dysfunction (e.g., jaundice). If these occur, promptly discontinue KYZATREX® while the cause is evaluated.

5.9 Edema

Androgens, including KYZATREX®, may promote retention of sodium and water. Edema, with or without congestive heart failure, may be a serious complication in patients with pre-existing cardiac, renal, or hepatic disease [see Adverse Reactions (6.1)]. In addition to discontinuation of the drug, diuretic therapy may be required.

5.10 Sleep Apnea

The treatment of hypogonadal men with testosterone may potentiate sleep apnea in some patients, especially those with risk factors such as obesity or chronic lung disease.

5.11 Gynecomastia

Gynecomastia may develop and persist in patients being treated for hypogonadism.

5.12 Lipid Changes

In clinical trials, patients receiving KYZATREX® experienced reductions in lipid parameters, including total cholesterol, LDL cholesterol, HDL cholesterol, and triglycerides [see Adverse Reactions (6.1)]. Changes in the serum lipid profile may require dose adjustment of lipid lowering drugs or discontinuation of testosterone therapy. Monitor the lipid profile periodically, particularly after starting testosterone therapy.

5.13 Hypercalcemia

Androgens, including KYZATREX®, should be used with caution in cancer patients at risk of hypercalcemia (and associated hypercalciuria). Monitor serum calcium concentrations periodically during treatment with KYZATREX® in these patients.

5.14 Descreased Thyroxine-binding Globulin

Androgens, including KYZATREX®, may decrease concentrations of thyroxin-binding globulin, resulting in decreased total T4 serum concentrations and increased resin uptake of T3 and T4. Free thyroid hormone concentrations remain unchanged, however, and there is no clinical evidence of thyroid dysfunction.

6 ADVERSE REACTIONS

The following clinically significant adverse reactions are discussed elsewhere in the labeling:

- Polycythemia [see Warnings and Precautions (5.1)]
- Venous Thromboembolism [see Warnings and Precautions (5.2)]
- Worsening of Benign Prostatic Hyperplasia (BPH) and Potential Risk of Prostate Cancer [see Warnings and Precautions (5.3)]
- Blood Pressure Increases [see Warnings and Precautions (5.4)]
- Hepatic Adverse Effects [see Warnings and Precautions (5.8)]
- Edema [see Warnings and Precautions (5.9)]
- Sleep Apnea [see Warnings and Precautions (5.10)]
- Gynecomastia [see Warnings and Precautions (5.11)]
- Lipid Changes [see Warnings and Precautions (5.12)]
- Hypercalcemia [see Warnings and Precautions (5.13)]
- Decreased Thyroxine-binding Globulin [see Warnings and Precautions (5.14)]

6.1 Clinical Trial Experience

Because clinical trials are conducted under widely varying conditions, adverse reaction rates observed in the clinical trials of a drug cannot be directly compared to rates in the clinical trials of another drug and may not reflect the rates observed in practice.

The safety of KYZATREX® was evaluated in Study MRS-TU-2019EXT in 155 hypogonadal males [see Clinical Studies (14)]. All patients initially received KYZATREX® 200 mg orally twice daily. If needed, the dosage was titrated to 100 mg once daily in the morning or 100 mg, 300 mg, or 400 mg twice daily to achieve testosterone concentrations in the normal range . After the dosage titration period, patients continued their optimized dose for the remainder of the duration of the 6-month study. The mean duration of exposure was 168 days (range: 1 to 180 days). The median age was 52 years (range: 22 to 66 years); 77% were White, 19% were Black, 3% were Asian, and 2% were American Indian, Alaskan Native or Other.

Table 2 summarizes adverse reactions reported in ≥2% of patients in this 6-month study.

Table 2: Adverse Reactions in ≥ 2% of Patients Receiving KYZATREX® in STUDY MRS-TU-2019EXT
Adverse Reaction | N = 155 n (%)
Hypertensión [Based upon blood pressure cuff measurements] | 4 (2.6)

One (0.8%) patient who received KYZATREX® experienced an adverse reaction (acne) that lead to premature discontinuation from the study.

In a 12-month, open-label study in hypogonadal adult males (N=212) who received KYZATREX® 200 mg once daily to 400 mg twice daily (n=202) the following additional adverse reactions were reported: headache, arthralgia, diarrhea, hemoglobin increased, anxiety, constipation, peripheral edema, and PSA increased.

Blood Pressure Increases

In Study MRS-TU-2019EXT, 24-hour ambulatory blood pressure monitoring (ABPM) was conducted in 155 male patients, 135 of whom completed the study. ABPM was conducted at 3 distinct 24-hour time periods: at baseline and following approximately 4 months and 6 months of treatment with KYZATREX®. A total of 151 patients had acceptable 24-hour ABPM recordings at both time periods. In that group, the mean change in systolic BP from Baseline to 4 months and 6 months was + 1.7 mm Hg (95% CI 0.3, 3.1) and 1.8 mm Hg (95% CI 0.3, 3.2), respectively. In that group, the mean change in diastolic BP from Baseline to 4 months and 6 months was 0.6 mm Hg (95% CI -0.3, 1.6) and 0.6 mm Hg (95% CI -0.4, 1.6), respectively. In patients with a history of hypertension on antihypertensive therapy at baseline, the mean ABPM systolic blood pressure increased from Baseline to 4 months and 6 months by 3.4 mm Hg (95% CI 1.0, 5.9) and 3.1 mm Hg (95% CI 0.6, 5.6), respectively (n=49).

In patients with no history of hypertension at baseline, the mean systolic blood pressure from Baseline increased by 0.7 mm Hg (95% CI -1.0, 2.4) at 4 months and 1.0 mm Hg (95% CI -0.7, 2.8), at six months respectively (n =90). Ambulatory (24-hour) blood pressure Changes from Baseline for study MRS- TU-2019EXT are presented in Table 3 with 95% confidence intervals. No significant difference was observed between the 4-month and 6-month Changes from Baseline

Table 3: Blood Pressure Increases
Blood Pressure | Change from Baseline (95% CI) mm Hg
Blood Pressure | Systolic | Diastolic
24-Hour Ambulatory
4 Month | 1.7 (0.3 to 3.1) | 0.6 (-0.3 to 1.6)
6 Month | 1.8 (0.3 to 3.2) | 0.6 (-0.4 to 1.6)

A history of antihypertensive treatment and diabetes mellitus at baseline were significant factors related to ambulatory SBP increases.

Table 4 presents the Least Squares Mean estimates of Change from Baseline, with 95% CI’s, for sub-populations of subjects at study start either with or without hypertensive treatment or with or without diabetes mellitus.

A total of 5 of 155 patients (3.2%) on KYZATREX® in Study MRS-TU-2019EXT began taking new antihypertensive medications after study start. No patient had a dose increase in their antihypertensive medication by the end of treatment.

Of the 155 patients in Study MRS-TU-2019EXT who used KYZATREX®, 4 patients (2.6%) were reported to have an adverse reaction of hypertension.

Cardiovascular Outcomes

TRAVERSE was a randomized, double-blind, cardiovascular outcomes study to assess the cardiovascular (CV) safety of topical testosterone gel compared to placebo in 5198 hypogonadal men aged 45 to 80 years with a history of CV disease or with multiple CV risk factors. The primary outcome was the incidence of the composite endpoint of major adverse cardiovascular events (MACE), consisting of CV death, non-fatal myocardial infarction (MI), and non-fatal stroke.

The mean duration of therapy was approximately 22 months. The mean duration of follow-up was 33 months. Approximately 61% of all patients discontinued topical testosterone gel or placebo therapy.

The mean patient age (±SD) was 63.3 (7.9) years, with 2452 patients ages 65 years or more (47%); 2847 (about 55%) patients had pre-existing cardiovascular disease, whereas 2357 patients (about 45%) had an elevated cardiovascular risk at baseline, and mean BMI was 35kg/m^2. Approximately 80% of patients were White, 17% were Black, and 3% were of other races or ethnic groups. Approximately 69%, 84%, and 93% had diabetes mellitus, hyperlipidemia, and hypertension, respectively.

The mean serum testosterone concentration at baseline in patients receiving topical testosterone gel was 220.4 ng/dL (n=2596). The mean serum testosterone concentrations at 12 months, 24 months, 36 months, and 48 months in patients receiving topical testosterone gel were 440.5 ng/dL (n=1683), 420.9 ng/dl (n=1125), 428.7 ng/dL (n=731), and 365.2 ng/dL (n=220), respectively.

For patients treated with topical testosterone gel, the incidence of MACE was 7.0% (n=182 events) and for those receiving placebo, the incidence of MACE was 7.3% (n=190 events). The study demonstrated non-inferiority of topical testosterone gel versus placebo because the upper bound of 95% CI was less than the pre-specified risk margin, of 1.5 for MACE (Hazard Ratio 0.96 [95% CI: 0.78, 1.17]).

Additional Adverse Reproted in TRAVERSE

Additional adverse reactions reported in TRAVERSE at an incidence rate >2% in either treatment group and greater in topical testosterone gel versus placebo included: nonfatal arrythmias warranting intervention (5.2% vs 3.3%), atrial fibrillation (3.5% vs 2.4%), acute kidney injury (2.3% vs 1.5%) and bone fracture (3.5% vs 2.5%). For the adverse reaction of bone fracture, each event was adjudicated by clinical review

Heart Rate Increases

KYZATREX® increased mean (95%CI) 24-hour ambulatory heart rate by an average of 0.7 (-0.5 to 1.9) beats per minute (bpm) at 4 months and 1.9 (0.6 to 3.1) bpm at 6 months in Study MRS-TU-2019EXT. Changes in heart rate were similar between patients with or without hypertension or diabetes. Changes in heart rate with treatment were most prominent in the evening, 12 to 17 hours after the morning dose.

Increases in Hemoglobin

Increases in hemoglobin were reported in 7 out of 155 patients (4.5%) in Study MRS-TU2019EXT. None of these increases led to premature discontinuation of KYZATREX®.

Hematocrit was not assessed in this study.

Headaches

Headaches were reported in 3 of 155 patients (1.9%) receiving KYZATREX® in Study MRSTU-2019EXT.

Increases in Serum PSA

Four out of 155 patients (2.6%) receiving KYZATREX® in Study MRS-TU-2019EXT had an increase in PSA from baseline greater than 1.4 ng/mL and two out of 155 patients (1.3%) had a PSA of at least 4.0 ng/mL during Study MRS-TU-2019EXT. The mean (SE) increase in PSA from baseline was 0.15 (±0.04) ng/mL at 6 months (n=135).

6.2 Postmarketing Experience

The following adverse reactions have been identified during post-approval use of testosterone. Because these reactions are reported voluntarily from a population of uncertain size, it is not always possible to reliably estimate their frequency or establish a causal relationship to drug exposure.

Cardiovascular Disorders: myocardial infarction, stroke
Vascular Disorders: Venous thromboembolism

7 DRUG INTERACTIONS

-

7.1 Insulin

Changes in insulin sensitivity or glycemic control may occur in patients treated with androgens. In diabetic patients, the metabolic effects of androgens may decrease blood glucose and therefore necessitate a decrease in the dose of anti-diabetic medication.

7.2 Oral Vitamin K Antagonist Anticoagulants

Changes in anticoagulant activity may be seen with androgens; therefore, more frequent monitoring of international normalized ratio (INR) and prothrombin time are recommended in patients taking warfarin, especially at the initiation and termination of androgen therapy.

7.3 Corticosteroids

The concurrent use of testosterone with corticosteroids may result in increased fluid retention and requires careful monitoring particularly in patients with cardiac, renal, or hepatic disease.

7.4 Medications that May Also Increase Blood Pressure

Some prescription medications and nonprescription analgesic and cold medications contain drugs known to increase blood pressure. Concomitant administration of these medications with KYZATREX® may lead to additional increases in blood pressure [see Warnings and Precautions (5.4)].

8 USE IN SPECIFIC POPULATIONS

-

8.1 Pregnancy

-

Risk Summary

KYZATREX® is contraindicated in pregnant women and not indicated for use in females [see Contraindications (4)]. Testosterone is teratogenic and may cause fetal harm when administered to a pregnant woman based on data from animal studies (see Data) and its mechanism of action [see Clinical Pharmacology (12.1)]. Exposure of a female fetus to androgens may result in varying degrees of virilization. In animal developmental studies, exposure to testosterone in utero resulted in hormonal and behavioral changes in offspring and structural impairments of reproductive tissues in female and male offspring. These studies do not meet current standards for nonclinical development toxicity studies.

Data

Animal Data

In developmental studies conducted in rats, rabbits, pigs, sheep, and rhesus monkeys, pregnant animals received intramuscular injections of testosterone during the period of organogenesis. Testosterone treatment at doses that were comparable to those used for testosterone replacement therapy resulted in structural impairments in both female and male offspring. Structural impairments observed in females included increased anogenital distance, phallus development, empty scrotum, no external vagina, intrauterine growth retardation, reduced ovarian reserve, and increased ovarian follicular recruitment. Structural impairments seen in male offspring included increased testicular weight, larger seminal tubular lumen diameter, and higher frequency of occluded tubule lumen. Increased pituitary weight was seen in both sexes.

Testosterone exposure in utero also resulted in hormonal and behavioral changes in offspring. Hypertension was observed in pregnant female rats and their offspring exposed to doses approximately twice those used for testosterone replacement therapy.

8.2 Lactation

-

Risk Summary

KYZATREX® is not indicated for use in females.

8.3 Females and Males of Reproductive Potential

-

Infertility

Males

During treatment with large doses of exogenous androgens, including KYZATREX®, spermatogenesis may be suppressed through feedback inhibition of the hypothalamicpituitary-testicular axis [see [See Warnings and Precautions (5.7) and Impairment of Fertility (13.1)] , possibly leading to adverse effects on semen parameters including sperm count. Reduced fertility has been observed in some men taking testosterone replacement therapy. Testicular atrophy, subfertility, and infertility have also been reported in men who abuse anabolic androgenic steroids [see Drug Abuse and Dependence (9.2)]. With either type of use, the impact on fertility may be irreversible.

8.4 Pediatric Use

The safety and efficacy of KYZATREX® in pediatric patients less than 18 years old have not been established. KYZATREX® is not recommended for use in patients less than 18 years of age because of the potential for acceleration of bone age and premature closure of epiphyses.

8.5 Geriatric Use

Clinical studies of KYZATREX® did not include any patients 65 years of age and older. Therefore, it cannot be determined whether these patients respond differently from younger adult patients. Additionally, there are insufficient long-term safety data in geriatric patients to assess the potentially increased risk of cardiovascular disease and prostate cancer.

Geriatric patients treated with androgens including KYZATREX® may be at risk for worsening of signs and symptoms of BPH [see (see Warnings and Precautions (5.3)].

9 DRUG ABUSE AND DEPENDENCE

-

9.1 Controlled Substance

KYZATREX® contains testosterone undecanoate, a Schedule III controlled substance

9.2 Abuse

Drug abuse is intentional non-therapeutic use of a drug, even once, for its rewarding psychological and physiological effects. Abuse and misuse of testosterone are seen in male and female adults and adolescents. Testosterone, often in combination with other anabolic androgenic steroids, and not obtained by prescription through a pharmacy, may be abused by athletes and bodybuilders. There have been reports of misuse by men taking higher doses of legally obtained testosterone than prescribed and continuing testosterone despite adverse events or against medical advice.

Abuse-Related Adverse Reactions

Serious adverse reactions have been reported in individuals who abuse anabolic androgenic steroids and include cardiac arrest, myocardial infarction, hypertrophic cardiomyopathy, congestive heart failure, cerebrovascular accident, hepatotoxicity, and serious psychiatric manifestations, including major depression, mania, paranoia, psychosis, delusions, hallucinations, hostility, and aggression.

The following adverse reactions have also been reported in men: transient ischemic attacks, convulsions, hypomania, irritability, dyslipidemias, testicular atrophy, subfertility, and infertility.

The following additional adverse reactions have been reported in women: hirsutism, virilization, deepening of voice, clitoral enlargement, breast atrophy, male-pattern baldness, and menstrual irregularities. The following adverse reactions have been reported in male and female adolescents: premature closure of bony epiphyses with termination of growth, and precocious puberty.

Because these reactions are reported voluntarily from a population of uncertain size and may include abuse of other agents, it is not always possible to reliably estimate their frequency or establish a causal relationship to drug exposure.

9.3 Dependence

Behaviors Associated with Addiction

Continued abuse of testosterone and other anabolic steroids leading to addiction is characterized by the following behaviors:

- Taking greater dosages than prescribed
- Continued drug use despite medical and social problems due to drug use
- Spending significant time to obtain the drug when supplies of the drug are interrupted
- Giving a higher priority to drug use than other obligations
- Having difficulty in discontinuing the drug despite desires and attempts to do so
- Experiencing withdrawal symptoms upon abrupt discontinuation of use

Physical dependence is characterized by withdrawal symptoms after abrupt drug discontinuation or a significant dose reduction of a drug. Individuals taking supratherapeutic doses of testosterone may experience withdrawal symptoms lasting for weeks or months, which may include depressed mood, major depression, fatigue, craving, restlessness, irritability, anorexia, insomnia, decreased libido, and hypogonadotropic hypogonadism.

Drug dependence in individuals using approved doses of testosterone for approved indications has not been documented.

10 OVERDOSAGE

There is one report of acute overdosage with use of an approved injectable testosterone product: this subject had serum testosterone levels of up to 11,400 ng/dL with a cerebrovascular accident.

Treatment of overdosage consists of discontinuation of KYZATREX® and appropriate symptomatic and supportive care.

11 DESCRIPTION

KYZATREX® is provided as a gelatin capsule containing testosterone undecanoate, a fatty-acid ester of testosterone. Testosterone undecanoate is a white to off-white yellow crystalline powder. Testosterone, an androgen, is formed by cleavage of the ester side chain of testosterone undecanoate.

Testosterone undecanoate is chemically described as 17β-hydroxyandrost-4-en-3-one undecanoate. It has the empirical formula of C30H48O3 and a molecular weight of 456.7 g/mol. The structural formula for testosterone undecanoate is presented in Figure 1.

Figure 1: Testosterone Undecanoate

KYZATREX® (testosterone undecanoate) capsules for oral use are available in three dosage strengths- 100 mg, 150 mg, and 200 mg. The 100 mg strength is an opaque, white capsule imprinted with "MP100" in red ink. The 150 mg strength is an opaque white capsule imprinted with "MP150" in red ink. The 200 mg strength is an opaque white capsule imprinted with "MP200" in red ink. All capsule strengths also contain DL-alpha-tocopheryl acetate (Vitamin E), phytosterol esters, polyoxyl 40 hydrogenated castor oil, and propylene glycol monolaurate as inactive ingredients.

Gelatin capsule shells are composed of the following inactive ingredients: gelatin, glycerin, purified water, sorbitol, and titanium dioxide.

12 CLINICAL PHARMACOLOGY

-

12.1 Mechanism of Action

Endogenous androgens, including testosterone and dihydrotestosterone (DHT), are responsible for the normal growth and development of the male sex organs and for maintenance of secondary sex characteristics. These effects include the growth and maturation of prostate, seminal vesicles, penis, and scrotum; the development of male hair distribution, such as facial, pubic, chest, and axillary hair; laryngeal enlargement; vocal cord thickening; alterations in body musculature; and fat distribution.

Male hypogonadism, a clinical syndrome resulting from insufficient secretion of testosterone, has two main etiologies. Primary hypogonadism is caused by defects of the gonads, such as Klinefelter syndrome or Leydig cell aplasia, whereas secondary hypogonadism (also known as hypogonadotropic hypogonadism) is the failure of the hypothalamus (or pituitary gland) to produce sufficient gonadotropins (FSH, LH).

12.2 Pharmacodynamics

There is insufficient data to characterize an exposure-response relationship or time course of pharmacodynamics.

12.3 Pharmacokinetics

-

Absorption

KYZATREX® was taken orally at a starting dose of 200 mg twice per day with meals in a multicenter, open-label trial in hypogonadal males. The dose was adjusted, as needed, on Days 28 and 56 from a minimum dose of 100 mg (morning-only) to a maximum dose of 400 mg twice per day based on the plasma testosterone concentration obtained by a single blood draw collected 3 to 5 hours after the morning dose. The average daily NaF/EDTA plasma testosterone concentration was 393.3 (±113.6) ng/dL after 90 days of treatment (normal eugonadal range in NaF/EDTA plasma: 222-800 ng/dL. Note that the titration scheme for use in clinical practice is based on serum total testosterone [see Dosage and Administration (2.2)] .

KYZATREX® is expected to produce testosterone concentrations that approximate normal concentrations seen in healthy men.

Table 5 summarizes the pharmacokinetic (PK) parameters for plasma total testosterone in patients completing at least 90 days of KYZATREX® treatment administered daily.

Table 5: NaF-EDTA Plasma Testosterone Cavg and Cmax at Day 90 Visit
PK Parameter |  | Plasma (N=130)
Cavg (ng/dL) | n | 127
Cavg (ng/dL) | Mean | 393.3
Cavg (ng/dL) | SD | 113.6
Cmax (ng/dL) | n | 130
Cmax (ng/dL) | Mean | 852.4
Cmax (ng/dL) | SD | 311.3
PK = pharmacokinetic; Cavg = 24-hour average concentration; Cmax = maximum concentration

Figure 2 summarizes the mean plasma total testosterone profile at the final PK visit.

Figure 2: Mean (±SEM) Concentration-Time Profile for NaF-EDTA Plasma Total Testosterone in KYZATREX®-Treated Patients at Day 90 Visit

SEM = standard error of the mean
Testosterone normal ranges: plasma = 222-800 ng/dL

When KYZATREX® was given with breakfast containing 16%, 33%, and 45% fat, the exposure (AUC0-24 hr) of testosterone was increased by 37%, 87%, and 94%, respectively, compared to when given under fasted conditions. The primary efficacy and safety study was conducted under fed conditions regardless of the type of meals and the primary efficacy endpoint of achieving testosterone Cavg in normal testosterone range was met.

There was no effect on testosterone PK when KYZATREX® was administered with 20% alcohol along with a high-fat meal versus a high-fat meal alone.

Distribution

Circulating testosterone is primarily bound in serum to sex hormone-binding globulin (SHBG) and albumin. Approximately 40% of testosterone in plasma is bound to SHBG, 2% remains unbound (free), and the rest is loosely bound to albumin and other proteins.

Metabolism

The androgenic activity of testosterone undecanoate occurs after the ester bond linking the testosterone to the undecanoic acid is cleaved by endogenous non-specific esterases.

Undecanoic acid is metabolized like all fatty acids via the beta-oxidation pathway.

Testosterone is metabolized to various 17-keto steroids through two different pathways. The major active metabolites of testosterone are dihydrotestosterone (DHT) and estradiol.

Excretion

About 90% of a dose of testosterone given intramuscularly is excreted in the urine as glucuronic and sulfuric acid conjugates of testosterone and its metabolites. About 6% of a dose is excreted in the feces, mostly in the unconjugated form. Inactivation of testosterone occurs primarily in the liver.

13 NONCLINICAL TOXICOLOGY

-

13.1 Carcinogenesis, Mutagenesis, Impairment of Fertility

-

Carcinogenesis

Testosterone has been tested by subcutaneous injection and implantation in mice and rats. In mice, the implant induced cervical-uterine tumors, which metastasized in some cases. There is suggestive evidence that injection of testosterone into some strains of female mice increases their susceptibility to hepatoma. Testosterone is also known to increase the number of tumors and decrease the degree of differentiation of chemically induced carcinomas of the liver in rats.

Mutagenesis

Testosterone was negative in the in vitro Ames and in the in vivo mouse micronucleus assays.

Impairment of Fertility

The administration of exogenous testosterone suppressed spermatogenesis and impaired fertility in the rat, dog, and non-human primate, which was reversible on cessation of treatment.

A reproductive toxicology study was conducted in rats to evaluate functional effects of KYZATREX® on male fertility. In untreated female rats mated with males receiving 2 times the maximum recommended human daily dose (MRHDD) of KYZATREX® (based on mean AUC exposure to testosterone), the number of impregnated females was reduced, fertility was significantly lower, and pre-implantation loss was significantly higher compared to the control group. There was no impairment of fertility in males receiving an equivalent dose of KYZATREX® to the MRHDD.

13.2 Animal Toxicology and/or Pharmacology

A 3-month repeat-dose oral toxicity study in male eugonadal dogs was conducted to evaluate whether phytosterol esters present in the KYZATREX® formulation influenced target organ toxicity due to their structural similarities to sex steroids like testosterone. KYZATREX® doses 2 times the MRHDD (based on mean AUC exposure to testosterone) produced similar effects on androgen-responsive tissues as testosterone undecanoate without phytosterol esters. These included mild to marked effects on the testes (decreased size, germ cell depletion, Leydig cell atrophy), epididymides (aspermia), adrenal glands (vacuolation in the zona fasciculata) and prostate (increased size and glandular hypertrophy/hyperplasia). Following a 4-week treatment-free period, findings in the testes, epididymides, and adrenal glands were not fully reversible at doses of 2 times the MRHDD of KYZATREX® as compared to treatment with the excipients alone, including phytosterol esters. Reversibility was not assessed in testosterone undecanoate groups without phytosterol esters.

14 CLINICAL STUDIES

The efficacy and safety of KYZATREX® were evaluated in Study MRS-TU-2019EXT (NCT04467697) a multi-center, open-label study of approximately 6 months of duration in 155 hypogonadal males.

Patients received KYZATREX® at a starting dose of 200 mg twice daily with meals. The dosage was adjusted on Days 28 and 56 between a minimum dose of 100 mg (single morning dose) and a maximum dose of 800 mg (400 mg twice daily) based on plasma testosterone concentration from a single blood draw between 3 to 5 hours after the morning dose.

The primary efficacy endpoint was the percentage of KYZATREX®-treated patients with mean plasma total testosterone concentration (Cavg) over 24-hours within the normal range of 222-800 ng/dL on the final PK visit of the study at Day 90.

The efficacy population consisted of 139 hypogonadal, males with a median age of 50 years (range 22 to 66 years), 79% were White, 16% were Black, 3% were Asian, and 2% were American Indian, Alaskan Native or Other.

Primary efficacy results are summarized in Table 6.

Table 6: Proportion of Patients in Study MRS-TU-2019EXT with Average Plasma Total Testosterone in the Normal Range (222-800 ng/dL) on Day 90
Parameter | N=139
Patients (%) with Testosterone, Cavg (ng/dL), 222-800 ng/dL | 122 (88%)
95% Confidence Interval | (82%, 93%)
Cavg = 24-hour average concentration

Secondary endpoints were the percentage of patients with a maximum total testosterone concentration (Cmax) meeting three predetermined limits: less than or equal to 1.5 times the upper limit of normal range (ULN) (1200 ng/dL), between 1.8 and 2.5 times ULN (1440-2000 ng/dL), and greater than 2.5 times ULN (2000 ng/dL).

The percentage of patients who received KYZATREX® and had testosterone Cmax threshold less than or equal to 1200 ng/dL, between 1440 and 2000 ng/dL, and greater than 2000 ng/dL at the final PK visit were 88%, 4%, and 0%, respectively.

16 HOW SUPPLIED/STORAGE AND HANDLING

KYZATREX® capsules are available in three strengths of 100 mg, 150 mg, and 200 mg packaged as 60, 90 and 120 units in wide-mouth, round, white HDPE bottles with white, polypropylene, child resistant caps and induction-sealed liner

100 mg: Oval, opaque, white capsules imprinted with "MP100" in red ink supplied in bottles; NDC 80603-101-11 for 90 capsules and NDC 80603-101-22 for 120 capsules.

150 mg: Oblong, opaque, white capsules imprinted with "MP150" in red ink supplied in bottles; NDC 80603-103-11 for 90 capsules and NDC 80603-103-22 for 120 capsules.

200 mg: Oblong, opaque, white capsules imprinted with "MP200" in red ink supplied in bottles; NDC 80603-105-33 for 60 capsules , NDC 80603-105-11 for 90 capsules and NDC 80603-105-22 for 120 capsules .

STORAGE AND HANDLING

Store at 20°C to 25°C (68°F to 77°F), with excursions permitted between 15°C to 30°C (59°F to 86°F) [see USP Controlled Room Temperature]. Store the capsules in a dry place avoiding exposure to excessive moisture and humid conditions.

Dispose of unused KYZATREX® via a take-back option. If a take-back option is unavailable, follow FDA instructions at www.fda.gov/drugdisposal.

17 PATIENT COUNSELING INFORMATION

Advise the patient to read the FDA-approved patient labeling (Medication Guide).

Polycythemia

Advise patients that KYZATREX® can cause an increase in hemoglobin/hematocrit levels that may increase the risk of thromboembolic events. Advise patients about the importance of completing laboratory testing as instructed by their health care provider while on KYZATREX® [see Warnings and Precautions (5.1)].

Venous Thromboebolisn

Advise patients that KYZATREX® can cause venous thromboembolism. Advise patients of the signs and symptoms of venous thromboembolism, which may include the following: lower limb pain, edema, or erythema; and dyspnea or chest pain. Advise patients to promptly report the signs and symptoms of venous thromboembolism, discontinue use of KYZATREX® and seek urgent medical care.

Worsening of Benign Prostatic Hyperplasia (BPH)

Advise patients that KYZATREX® can cause increased symptoms of BPH. Advise patients to contact their health care provider if they have any prostate-related symptoms [see Warnings and Precautions (5.3)].

Blood Pressure Increases

Inform patients that KYZATREX® can increase blood pressure (BP) which can increase cardiovascular risk over time Instruct patients about the importance of monitoring BP periodically while on KYZATREX®. If BP increases while on KYZATREX®, antihypertensive medications may need to be started, added, or adjusted to control BP, or KYZATREX® may need to be discontinued [see Warnings and Precautions (5.4)]

Edema

Advise patients that KYZATREX® can cause edema in patients with preexisting cardiac, renal, or hepatic disease. Advise patients to notify their health care provider if edema develops or worsens [see Warnings and Precautions (5.9)].

Sleep Apnea

Advise patients that KYZATREX® can worsen sleep apnea especially in patients with risk factors such as obesity or chronic lung diseases ™ [see Warnings and Precautions (5.10)].

Gynecomastia

Advise patients that KYZATREX® can cause gynecomastia [see Warnings and Precautions (5.11)].

Administration Instructions

Advise patients to take KYZATREX® with food [see Dosage and Administration (2.3)].

Marketed by:
Marius Pharmaceuticals
2301 Suger Bush Road, Suite 510

Raleigh, NC 27612

Issued 07/2025

MEDICATION GUIDE
KYZATREX® (ky-ZAH-treks)
(testosterone undecanoate) capsules, for oral use, CIII

What is KYZATREX® ?

- KYZATREX ® is a prescription medicine that contains testosterone. KYZATREX ® is used to treat adult men who have low or no testosterone due to certain medical conditions.
- It is not known if KYZATREX ® is safe or effective in children younger than 18 years old. Improper use of KYZATREX ® may affect bone growth in children.
- KYZATREX ® is a controlled substance (CIII) because it contains testosterone that can be a target for people who abuse prescription medicines. Keep your KYZATREX ® in a safe place to protect it. Never give your KYZATREX ® to anyone else, even if they have the same symptoms you have. Selling or giving away this medicine may harm others and is against the law.
- KYZATREX ® is not meant for use by women.

Do not take KYZATREX® if you:

- have breast cancer.
- have or might have prostate cancer.
- are a woman who is pregnant. KYZATREX ® may harm your unborn baby.
- are allergic to KYZATREX ® or any ingredients in KYZATREX ®. See the end of this Medication Guide for a complete list of ingredients in KYZATREX ®.

Before you take KYZATREX®, tell your healthcare provider about all of your medical conditions, including if you:

- have high blood pressure or are being treated for high blood pressure.
- have a history of diabetes.
- have heart problems.
- have high red blood cell count (hematocrit) or high hemoglobin laboratory value.
- have urinary problems due to an enlarged prostate.
- have liver or kidney problems.
- have problems breathing while you sleep (sleep apnea).

Tell your healthcare provider about all the medicines you take, including prescription and over-the-counter medicines, vitamins, and herbal supplements. Taking KYZATREX ® with certain other medicines can affect each other.
Especially, tell your healthcare provider if you take:

- insulin
- medicines that decrease blood clotting (blood thinners)
- corticosteroids
- medicines that increase blood pressure such as some cold medicine and pain medicines

Know the medicines you take. Ask your healthcare provider or pharmacist for a list of these medicines, if you are not sure. Keep a list of them and show it to your healthcare provider and pharmacist when you get a new medicine.

How should I take KYZATREX®?

- Take KYZATREX ® exactly as your healthcare provider tells you take it.
- Take KYZATREX ® by mouth 2 times daily. Take 1 time in the morning and take 1 time in the evening. If your dose is 100 mg daily, take 1 time in the morning.
- Take KYZATREX ® with food.
- Your healthcare provider may change your KYZATREX ® dose. Do not change your KYZATREX ® dose without talking to your healthcare provider.

What are the possible side effects of KYZATREX®?
KYZATREX® may cause serious side effects including:

- See " What is the most important information I should know about KYZATREX®?"
- Increase in red blood cell count (hematocrit) or hemoglobin.
  - KYZATREX ® increases red blood cell counts in some patients. High red blood cell counts increase the risk of blood clots, strokes, and heart attacks.
  - You may need to stop KYZATREX ® if your red blood cell count increases.
  - Your healthcare provider should check your red blood cell count and hemoglobin while you take KYZATREX ®.
- If you already have an enlarged prostate, your signs and symptoms may worsen while taking KYZATREX®.
  - These may include:
  - increased urination at night
  - trouble starting your urine stream
  - urinating many times during the day
  - urge to go to the bathroom right away
  - a urine accident
  - inability to pass urine or weak urine flow
- Increased risk of prostate cancer. Your healthcare provider should check you for prostate cancer or any other prostate problems before you start and while you take KYZATREX ®.
- Blood clots in the legs or lungs. Signs and symptoms of a blood clot in your leg can include pain, swelling or redness. Signs and symptoms of a blood clot in your lungs can include difficulty breathing or chest pain. Increase in blood pressure. KYZATREX® can increase your blood pressure. Increases in blood pressure can increase the risk of heart attack or stroke over time. If your blood pressure increases while on KYZATREX®, blood pressure medicines may need to be started. If you are taking blood pressure medicines, new blood pressure medicines may need to be added or your current blood pressure medicines may need to be adjusted to control your blood pressure. If your blood pressure cannot be controlled, KYZATREX® may need to be stopped. Your healthcare provider will monitor your blood pressure while you are being treated with KYZATREX®
- Abuse. Testosterone can be abused, when taken at higher than prescribed doses and when used with other anabolic androgenic steroids. Abuse can cause serious heart and psychological side effects. Your healthcare provider should check you for signs of abuse before and during treatment with KYZATREX®.
- In large doses KYZATREX® may lower your sperm count.
- Liver problems.Symptoms of liver problems may include:
  - nausea or vomiting
  - yellowing of your skin or whites of your eyes
  - dark urine
  - pain on the right side of your stomach area (abdominal pain)
- Swelling of your ankles, feet, or body (edema), with or without heart failure.
- Enlarged or painful breasts.
- Breathing problems while you sleep (sleep apnea).

Call your healthcare provider right away if you have any of the serious side effects listed above.
The most common side effect of KYZATREX® is high blood pressure.
Other side effects may include headache, joint or back pain, diarrhea, increased red blood cell count, anxiety, constipation, swelling of the legs, and increased prostate specific antigen (PSA) levels.
Tell your healthcare provider if you have any side effect that bothers you or that does not go away.
These are not all the possible side effects of KYZATREX®. For more information, ask your healthcare provider or pharmacist.
Call your doctor for medical advice about side effects. You may report side effects to FDA at 1-800-FDA-1088.

How should I store KYZATREX®?

- Store KYZATREX® at room temperature between 68°F to 77°F (20°C to 25°C).
- Store KYZATREX® in a dry place.

Keep KYZATREX® and all medicines out of the reach of children.
How should I throw away (dispose of) KYZATREX®?

- Throw away unused KYZATREX® via a take-back option.
- If a take-back option is unavailable, follow FDA instructions at www.fda.gov/drugdisposal for properly throwing away medicine.

General information about the safe and effective use of KYZATREX®
Medicines are sometimes prescribed for purposes other than those listed in a Medication Guide. Do not use KYZATREX® for a condition for which it was not prescribed. Do not give KYZATREX® to other people, even if they have the same symptoms you have. It may harm them. You can ask your pharmacist or healthcare provider for information about KYZATREX® that is written for health professionals.

What are the ingredients in KYZATREX®?
Active ingredient: testosterone undecanoate
Inactive ingredients: DL-alpha-tocopheryl acetate (Vitamin E), phytosterol esters, polyoxyl 40 hydrogenated castor oil and propylene glycol monolaurate. The ingredients of the gelatin capsule shells are gelatin, glycerin, purified water, sorbitol, and titanium dioxide.
Marketed by:
Marius Pharmaceuticals
Raleigh, NC 27612
For more information, go to www.KYZATREX.com or call 1-833-949-5040

This Medication Guide has been approved by the U.S. Food and Drug Administration

Issued: 07/2025